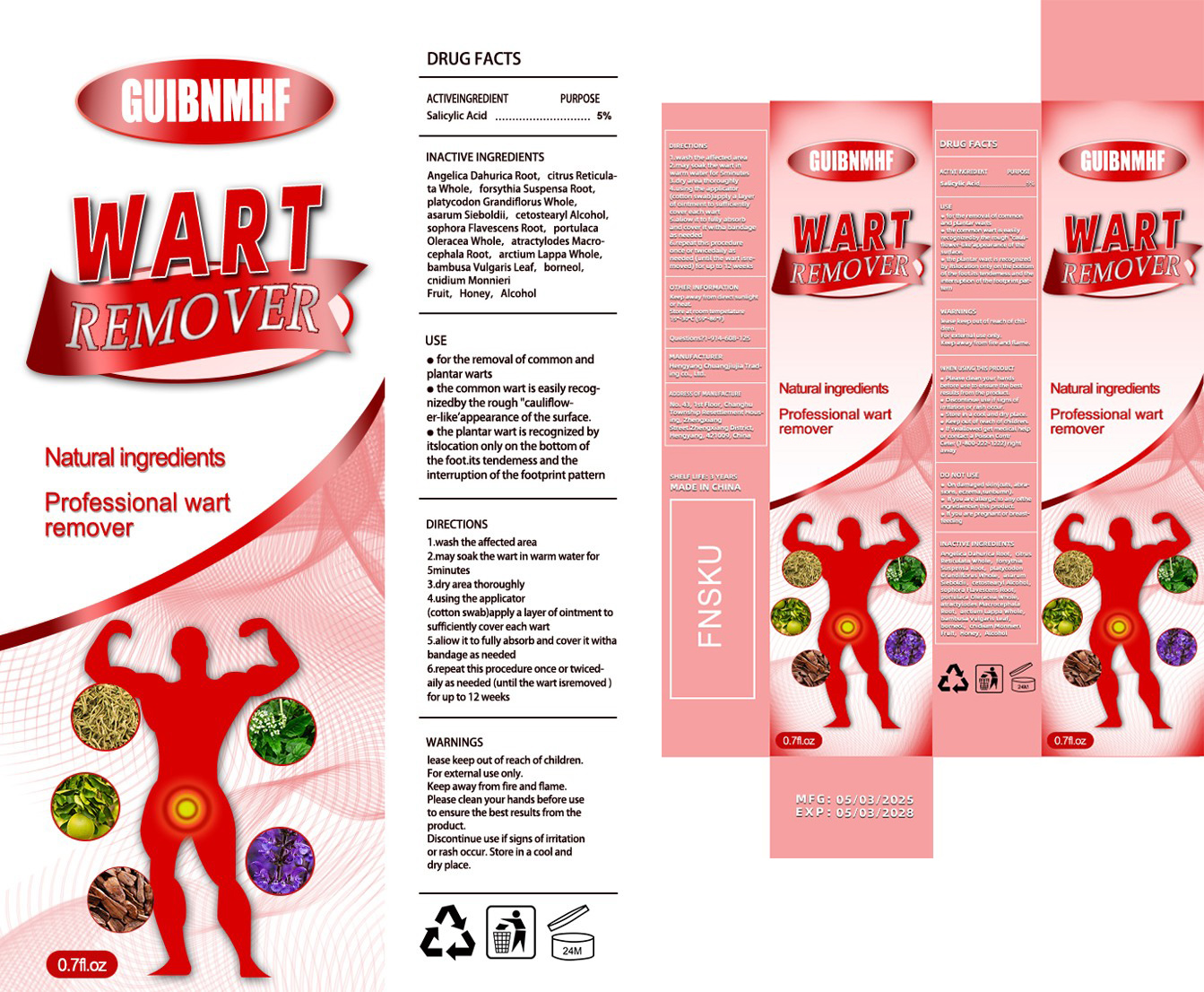 DRUG LABEL: wart remover
NDC: 84735-007 | Form: CREAM
Manufacturer: Hengyang Chuangjiujia Trading Co., Ltd.
Category: otc | Type: HUMAN OTC DRUG LABEL
Date: 20250507

ACTIVE INGREDIENTS: SALICYLIC ACID 5 g/100 g
INACTIVE INGREDIENTS: ALCOHOL; ANGELICA DAHURICA ROOT; FORSYTHIA SUSPENSA ROOT; BAMBUSA VULGARIS LEAF; CNIDIUM MONNIERI FRUIT; HONEY; SOPHORA FLAVESCENS ROOT; ARCTIUM LAPPA WHOLE; ASARUM SIEBOLDII; CETOSTEARYL ALCOHOL; ATRACTYLODES MACROCEPHALA ROOT; CITRUS RETICULATA WHOLE; PLATYCODON GRANDIFLORUS WHOLE; PORTULACA OLERACEA WHOLE; BORNEOL

84735-007 wart remover

ACTIVE INGREDIENT

Salicylic Acid 5%

PURPOSE

Wart remover

INDICATIONS AND USAGE

for the removal of common andplantar warts
the common wart is easily recog-nizedby the rough "cauliflow-er-like'appearance of the surface.
the plantar wart is recognized byitslocation only on the bottom ofthe foot.its tendemess and theinterruption of the footprint pattern

WARNINGS

lease keep out ofreach ofchildren.For extemal use only.Keep away from fire and flame.Please clean your hands before useto ensure the best results from theproduct.Discontinue use if signs ofirritationor rash occur. Store in a cool anddry place.

WHEN USING

Please clean your hands before use to ensure the best results from theproduct.

Discontinue use if signs ofirritationor rash occur.

lease keep out ofreach ofchildren.

DOSAGE AND ADMINISTRATION

1.wash the affected area
2.may soak the wart in wam water for 5 minutes
3.dry area thoroughly
4.using the applicator(cotton swab) apply a layer of ointment tosuficiently cover each wart
5.aliow it to fully absorb and cover it withabandage as needed
6.repeat this procedure once or twiced-aily as needed (until the wart isremoved)for up to 12 weeks

INACTIVE INGREDIENT

ANGELICA DAHURICA ROOT
CITRUS RETICULATA WHOLE
FORSYTHIA SUSPENSA ROOT
PLATYCODON GRANDIFLORUS WHOLE
ASARUM SIEBOLDII
CETOSTEARYL ALCOHOL
SOPHORA FLAVESCENS ROOT
PORTULACA OLERACEA WHOLE
ATRACTYLODES MACROCEPHALA ROOT
ARCTIUM LAPPA WHOLE
BAMBUSA VULGARIS LEAF
BORNEOL
CNIDIUM MONNIERI FRUIT
HONEY
ALCOHOL